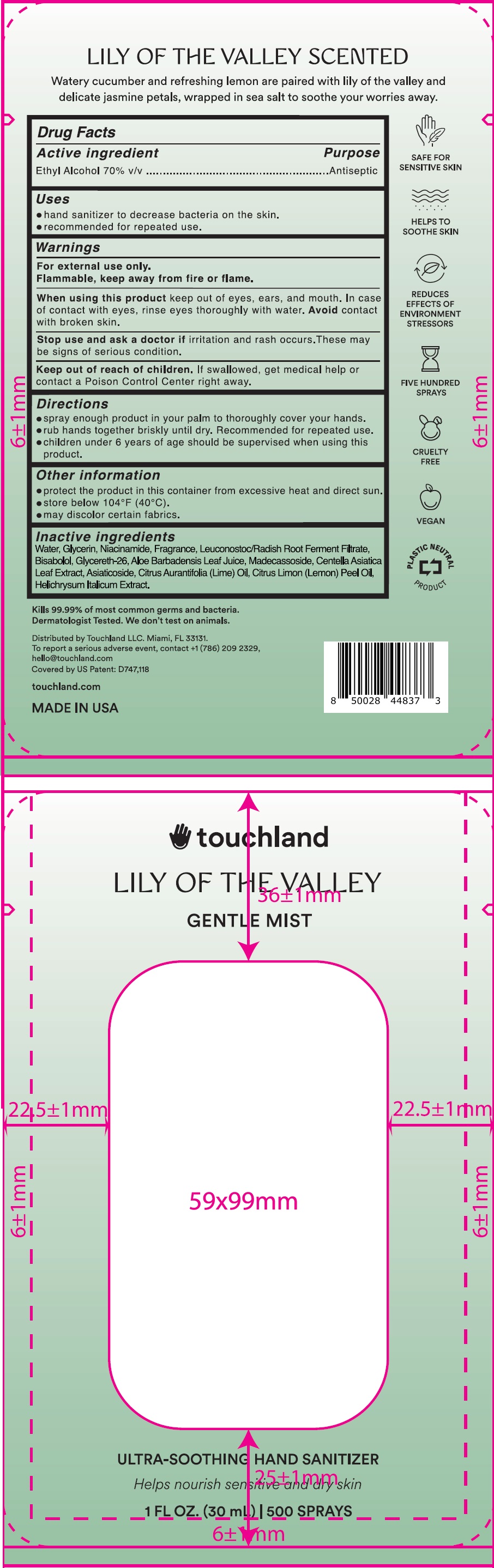 DRUG LABEL: Touchland Gentle Mist Ultra Soothing Hand Lily of The Valley
NDC: 72033-217 | Form: SPRAY
Manufacturer: TOUCHLAND LLC
Category: otc | Type: HUMAN OTC DRUG LABEL
Date: 20231228

ACTIVE INGREDIENTS: ALCOHOL 70 mg/100 mL
INACTIVE INGREDIENTS: WATER; GLYCERIN; NIACINAMIDE; LEUCONOSTOC/RADISH ROOT FERMENT FILTRATE; LEVOMENOL; GLYCERETH-26; ALOE VERA LEAF; MADECASSOSIDE; CENTELLA ASIATICA LEAF; ASIATICOSIDE; LIME OIL, COLD PRESSED; LEMON OIL, COLD PRESSED; HELICHRYSUM ITALICUM FLOWER

Touchland Gentle Mist Ultra Soothing Hand Lily of The Valley

Active ingredient

Ethyl Alcohol 70% v/v

Purpose

Antispetic

Uses

• hand sanitizer to decrease bacteria on the skin. • recommended for repeated use.

Warnings

For external use only.
Flammable, keep away from fire or flame.

When using this product

keep out of eyes, ears, and mouth. In case of contact with eyes, rinse eyes throughly with water. Avoid contact with broken skin.

Stop use and ask a doctor if

irritation and rash occurs. These may be signs of serious condition.

Keep out of reach of children.

If swallowed, get medical help or contact a Poison Control Center right away.

Directions

• spray enough product in your palm to throughly cover your hands. • rub hands together briskly until dry. Recommended for repeated use. • children under 6 years of age should be supervised when using this product.

Other information

• protection the product in this container from excessive heat and direct sun. • store below 104°F (40°C). • may discolor certain fabrics.

Inactive ingredients

Water, Gycerin, Niacinamide, Fragrance, Leuconostoc/Radish Root Ferment Filtrate, Bisabolol, Glycereth-26, Aloe Barbadensis Leaf Juice, Madecassoside, Centella Asiatica Leaf Extract, Asiaticoside, Citrus Aurantifolia (Lime) Oil, Citrus Limon (Lemon) Peel Oil, Helichrysum Italicum Extract.